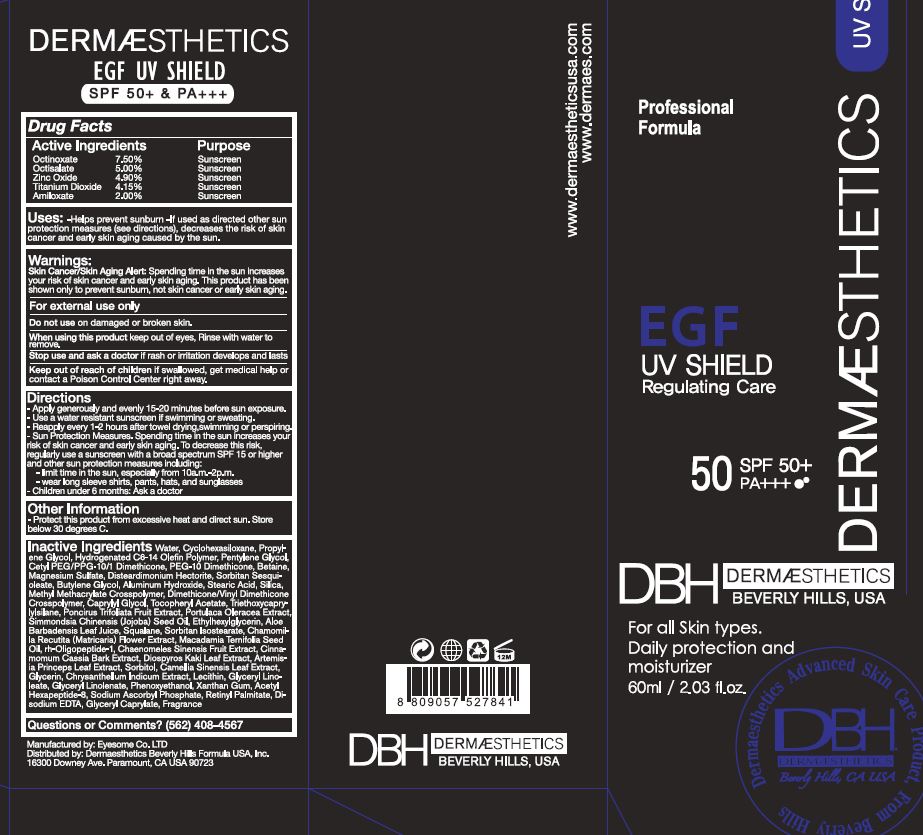 DRUG LABEL: EGF UV SHIELD
NDC: 58831-2001 | Form: CREAM
Manufacturer: Dermaesthetics Inc.
Category: otc | Type: HUMAN OTC DRUG LABEL
Date: 20191222

ACTIVE INGREDIENTS: OCTINOXATE 7.5 g/100 mL; OCTISALATE 5 g/100 mL; ZINC OXIDE 0.9 g/100 mL; TITANIUM DIOXIDE 4.15 g/100 mL; AMILOXATE 2 g/100 mL
INACTIVE INGREDIENTS: WATER; TRIEPOXYCYCLOHEXASILANE

EGF UV Shield

Drug Fact

Active ingredient
Octinoxate 7.50%
Octisalate 5.00%
Zinc Oxide 4.90%
Titanium Dioxide 4.15%
Amiloxate 2.00%

Purpose

Sunscreen

Keep out of reach of children

Stop use and ask a doctor
if rash or irritation develops and lasts.

Keep out of reach of children
if swallowed, get medical help or contact a Poison Control Center right away.

Indication & usage

Directions
-Apply generously and evenly 15-20 minutes before sun exposure.

-Use a water resistant sunscreen if swimming or sweating.

-Reapply every 1-2 hours after towel drying, swimming or perspiring.

-Sun Protection Measures.

Spending time in the sun increases your risk of skin cancer and early skin aging.

To decrease this risk, regularly use a sunscreen with a broad spectrum SPF of 15 or higher and other sun protection measures

including:

- limit time in the sun, especially from 10 a.m. ~ 2 p.m.

- wear long-sleeve shirts, pants, hats, and sunglasses

-Children under 6 months: Ask a doctor

Warning

Warnings

Skin Cancer/Skin Aging Alert:

Spending time in the sun increases your risk of skin cancer and early skin aging.

This product has been shown only to prevent sunburn, not skin cancer or early skin aging.

For external use only.

Do not use on damaged or broken skin. If sun irritation develops or increases.

When using this product keep out of eyes. Rinse with water to remove.

Dosage & administration

for external use only

Inactive ingredient

Water, Propylene Glycol, Cyclopentasiloxane, Hydrogenated Poly(C6-14 Olefin Polymer), pentylent glycol, Cetyl PEG/PPG-10/1 Dimethicone, PEG-10 Dimethicone, Betaine, Magnesium Sulfate, Disteardimonium Hectorite, Sorbitan Sesquioleate, butylene glycol, Aluminum Hydroxide, Stearic Acid, silica Dimethicone/Vinyl Dimethicone Crosspolymer, Methyl Methacrylate Crosspolymer, caprylyl glycol, tocopheryl acetate, Triethoxycaprylylsilane, Portulaca Oleracea Extract, Poncirus Trifoliata Fruit Extract, Tocopheryl Acetate, jojoba seed oil, ethyhexylglycerin, Aloe Barbadensis Leaf Juice, squalane, sorbitan isostearate, chamomilla recutita (matricaria) flower extract, macadamia ternifolia seed oil, rh-oligopeptide-1, chaenomeles sinensis fruit extract, cinnamomum cassia bark extract, diospyros kaki leaf extract, artemisia princeps leaf extract, sorbitol, camellia sinensis leaf extract, glycerin, chrysanthellum indicum extract, lecithin, glyceryl linoleate, glyceryl linolenate, phenoxyethano, xanthan gum, acetyl hexapeptide-8, sodium ascorbyl phosphate, retinyl palmitate, di-sodium edta, glyceryl caprylate, fragrance